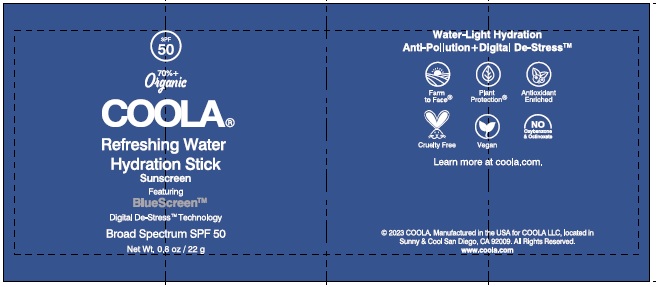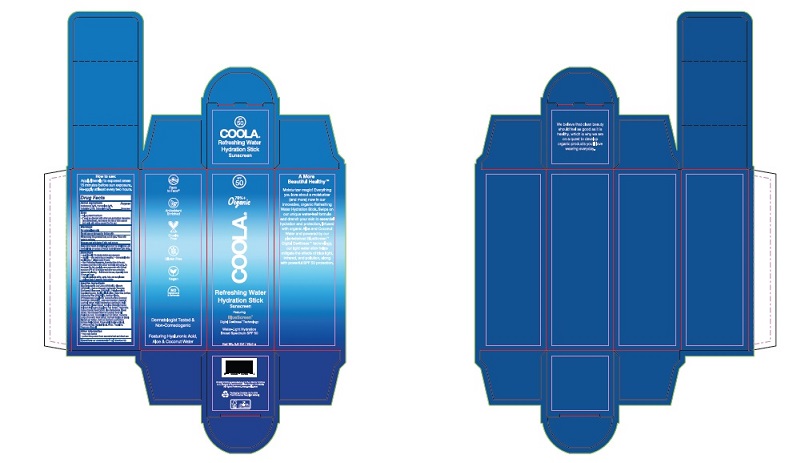 DRUG LABEL: Refreshing Water Hydration Stick
NDC: 79753-035 | Form: STICK
Manufacturer: COOLA LLC
Category: otc | Type: HUMAN OTC DRUG LABEL
Date: 20241227

ACTIVE INGREDIENTS: AVOBENZONE 2.5 g/100 g; OCTISALATE 2.15 g/100 g; HOMOSALATE 3.5 g/100 g; OCTOCRYLENE 5.0 g/100 g
INACTIVE INGREDIENTS: ALOE VERA LEAF; GLYCERIN; SODIUM STEARATE; CARTHAMUS TINCTORIUS (SAFFLOWER) OLEOSOMES; POLYGLYCERYL-10 CAPRYLATE; POLYGLYCERYL-10 CAPRATE; BUTYLOCTYL SALICYLATE; CARNAUBA WAX; SORBITAN OLIVATE; VINYLPYRROLIDONE/HEXADECENE COPOLYMER; PROPANEDIOL; BUTYLENE GLYCOL; 1,2-HEXANEDIOL; CAPRYLYL GLYCOL; WATER; JASMINUM OFFICINALE LEAF; AZADIRACHTA INDICA LEAF; AZADIRACHTA INDICA FLOWER; CORALLINA OFFICINALIS; COCCINIA GRANDIS FRUIT; TROPOLONE; EGGPLANT; COCOA; ALOE VERA FLOWER; COCONUT WATER; JOJOBA OIL; TURMERIC; OCIMUM BASILICUM FLOWERING TOP; HOLY BASIL LEAF; SCHINUS MOLLE FRUITING TOP; HYALURONIC ACID

COOLA Refreshing Water Hydration Stick SPF 50

Drug Facts

Active Ingredients

Avobenzone 2.5%, Homosalate 3.5%, Octisalate 2.15%, Octocrylene 5.0%

Purpose

Suncreen

Uses

- helps prevent sunburn

- if used as directed with other sun protection measures

(see Directions), decreases the risk of skin cancer and early skin aging caused by the sun

Warnings

For external use only

Do not use on damaged or broken skin

When using this product keep out of eyes. Rinse with water to remove.

Stop use and ask doctor if skin rash occurs

Keep out of reach of children. If product is swallowed, get

medical help or contact a Poison Control Center right away.

Directions
●apply liberally 15 minutes before sun exposure.
● reapply: ●after swimming or sweating ● immediately afte
towel drying ● at least every 2 hours

● Sun Protection Measures. Spending time in the sun increases your risk of skin cancer
and early skin aging. To decrease this risk, regularly use a sunscreen with a broad spectrum
SPF of 15 or higher and other sun protection measures including:
● limit time in the sun, especially from: 10 a.m. - 2 p.m.
● wear long-sleeve shirts, pants, hats, and sunglasses
●Children under 6 months: Ask a doctor

Inactive Ingredients

Aloe Barbadensis Leaf Juice (ORGANIC), Glycerin (ORGANIC), Sodium Stearate, Carthamus Tinctorius (Safflower) Oleosomes (ORGANIC), Polyglyceryl-10 Caprylate/Caprate, Butyloctyl Salicylate, Copernicia Cerifera (Carnauba) Wax (ORGANIC), Sorbitan Olivate, VP/Hexadecene Copolymer, Cocos Nucifera (Coconut) Fruit Water (ORGANIC), Jasminum Sambac (Jasmine) Leaf Cell Extract, Melia Azadirachta Leaf Extract, Melia Azadirachta Flower Extract, Coralline Officinalis Extract, Solanum Melongena (Eggplant) Fruit Extract, Theobroma Cacao (Cocoa) Seed Extract, Aloe Barbadensis Flower Extract, Simmondsia Chinensis (Jojoba) Seed Oil, Hyaluronic Acid, Coccinia Indica Fruit Extract, Curcuma Longa (Turmeric) Root Extract, Ocimum Basilicum (Basil) Flower/Leaf Extract, Ocimum Sanctum Leaf Extract, Schinus Molle Extract, Propanediol, Butylene Glycol, 1,2-Hexanediol, Caprylyl Glycol, Water, Tropolone, Fragrance (Natural)

Other information

- may stain fabrics
- protect this product from excessive heat and direct sun

Questions or comments?
Call 760-940-2125

COOLA Label

SPF

50

70%+

Organic

COOLA®

Refreshing Water

Hydration Stick

Sunscreen

Net Wt. 0.8 OZ / 22.0 g

©2023 COOLA. Manufactured in the USA for COOLA

LLC, located in Sunny & Cool San Diego, CA 92010.

All Rights Reserved. www.coola.com

res